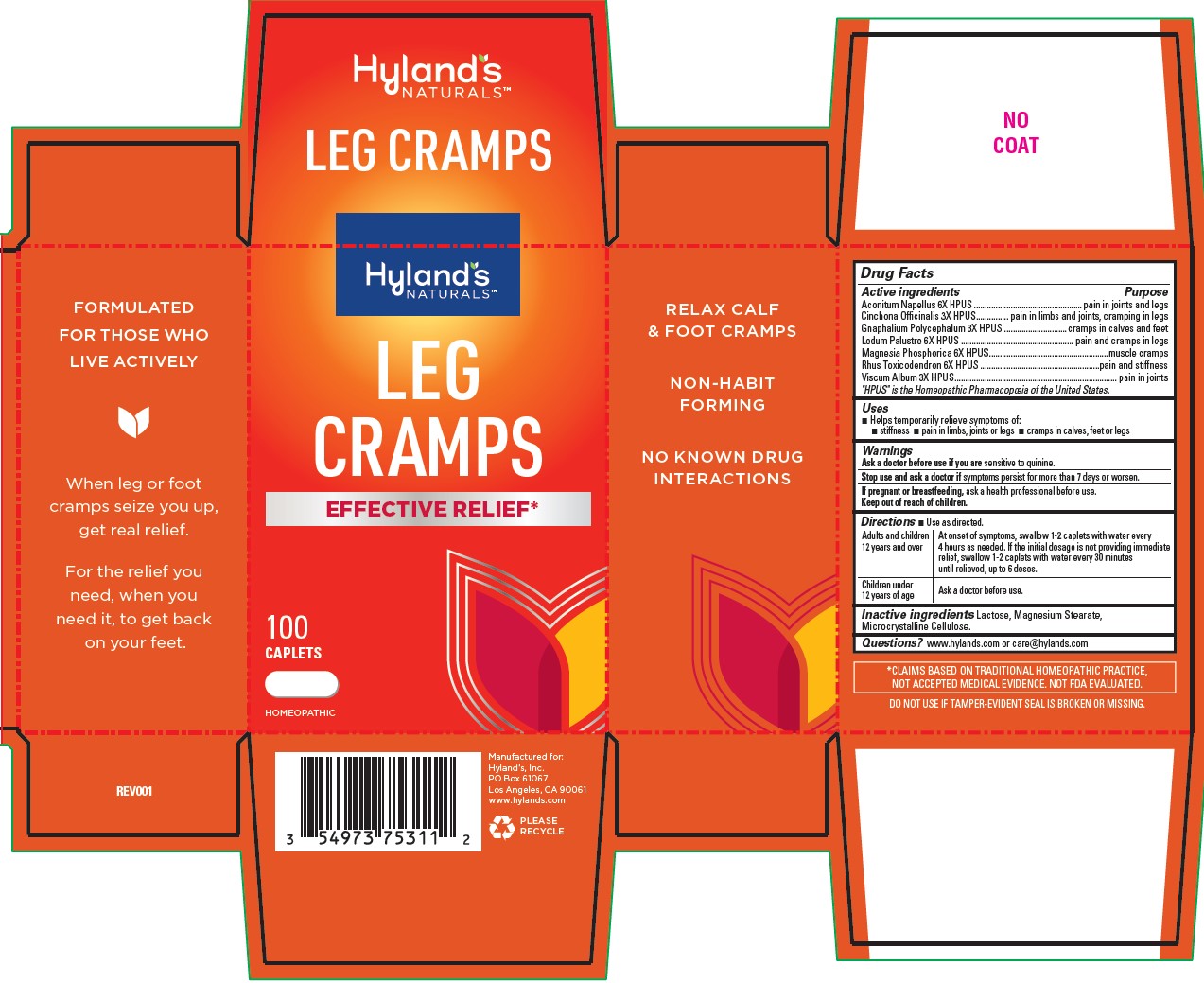 DRUG LABEL: LEG CRAMPS
NDC: 54973-3114 | Form: TABLET, SOLUBLE
Manufacturer: Hyland's Inc.
Category: homeopathic | Type: HUMAN OTC DRUG LABEL
Date: 20221102

ACTIVE INGREDIENTS: CINCHONA OFFICINALIS BARK 3 [hp_X]/1 1; ACONITUM NAPELLUS 6 [hp_X]/1 1; PSEUDOGNAPHALIUM OBTUSIFOLIUM 3 [hp_X]/1 1; LEDUM PALUSTRE TWIG 6 [hp_X]/1 1; MAGNESIUM PHOSPHATE, DIBASIC TRIHYDRATE 6 [hp_X]/1 1; TOXICODENDRON PUBESCENS LEAF 6 [hp_X]/1 1; VISCUM ALBUM FRUITING TOP 3 [hp_X]/1 1
INACTIVE INGREDIENTS: LACTOSE; CELLULOSE, MICROCRYSTALLINE; MAGNESIUM STEARATE

Leg Cramps Caplets

PURPOSE

Temporarily relieves the symptoms of stiffness, pains in limbs, joints, legs and cramps in calves, feet and legs.

Drug Facts

Active ingredients | Purpose
Aconitum Napellus 6X HPUS | pains in joints and legs
Cinchona Officinalis 3X HPUS | pains in limbs and joints; cramping in legs
Gnaphalium Polycephalum 3X HPUS | cramps in calves and feet
Ledum Palustre 6X HPUS | pain and cramps in legs
Magnesia Phosphorica 6X HPUS | muscle cramps
Rhus Toxicodendron 6X HPUS | pain and stiffness
Viscum Album 3X HPUS | pains in joints

"HPUS" indicates the active ingredients are in the official Homeopathic Pharmacopœia of the United States.

Warnings

Ask a doctor before use if you are

sensitive to quinine.

If pregnant or breastfeeding

ask a health professional before use.

Stop use and ask a doctor if

symptoms persist for more than 7 days or worsen.

Directions

■ Use as directed.

Adults and children 12 years and over | At onset of symptoms, swallow 1-2 caplets with water every 4 hours as needed. If the initial dosage is not providing immediate relief, swallow 1-2 caplets with water every 15 minutes until relieved, up to 6 doses.
Children under 12 years of age | Ask a doctor before use.

Inactive ingredients

Lactose, Magnesium Stearate, Microcrystalline Cellulose.

Questions?

www.hylands.com or care@hylands.com

Dosage and Administration

Adults and children; 12 years and over | Swallow 1-2 caplets with water every 4 hours. If the initial dosage is; not providing relief, swallow 1-2 caplets with water every 15 minutes,; up to 6 doses.
Under 12 years of age | Consult a physician.

Indications and Usage

■ Temporarily relieves the symptoms of:

■ stiffness ■ pain in limbs, joints or legs ■ cramps in calves, feet or legs

Uses

■ Helps temporarily relieve symptoms of:

■ stiness ■ pain in limbs, joints or legs ■ cramps in calves, feet or legs

Principal Display Panel

Hyland's

NATURALS

LEG

CRAMPS

EFFECTIVE RELIEF*

100

CAPLETS

HOMEOPATHIC